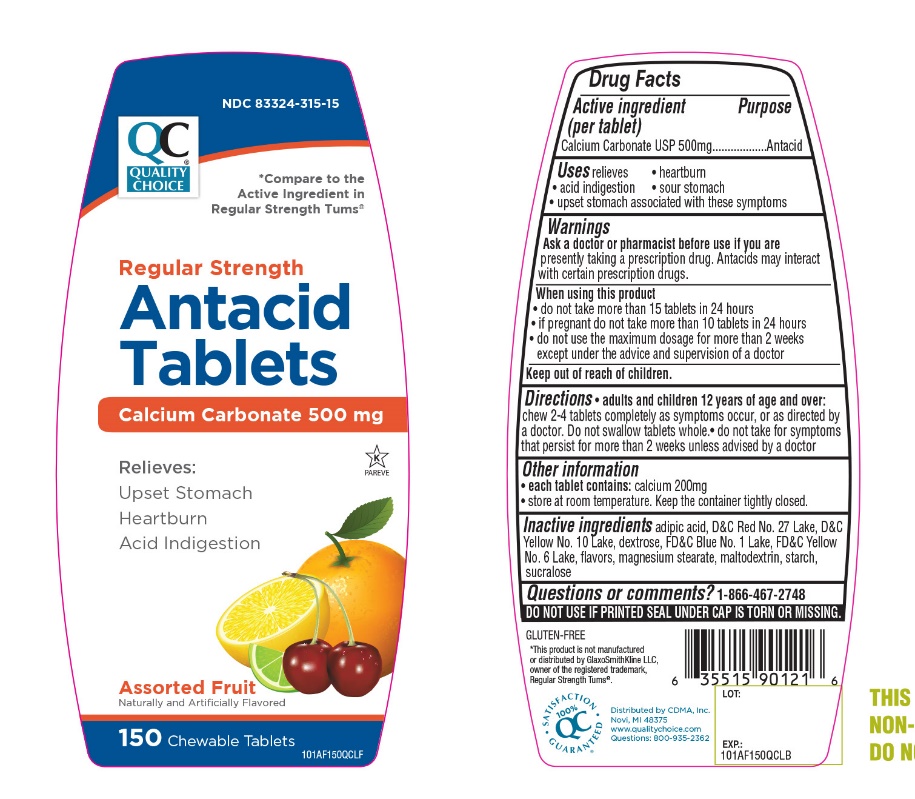 DRUG LABEL: QUALITY CHOICE

NDC: 83324-315 | Form: TABLET, CHEWABLE
Manufacturer: QUALITY CHOICE (Chain drug Marketing Assoiciation)
Category: otc | Type: HUMAN OTC DRUG LABEL
Date: 20251204

ACTIVE INGREDIENTS: CALCIUM CARBONATE 500 mg/1 1
INACTIVE INGREDIENTS: ADIPIC ACID; D&C RED NO. 27; D&C YELLOW NO. 10; DEXTROSE, UNSPECIFIED FORM; FD&C BLUE NO. 1; FD&C YELLOW NO. 6; MAGNESIUM STEARATE; MALTODEXTRIN; STARCH, CORN; SUCRALOSE

Drug Facts

Active ingredient

Calcium carbonates USP 500mg

Purpose

Antacid

Uses

relieves:

- heartburn
- sour stomach
- acid indigestion
- upset stomach associated with these symptoms

Warnings

Ask a doctor or pharmacist before use if you aretaking a prescription drug. Antacids may interact with certain prescription drugs.

When using this product

- do not take more than 15 tablets in 24 hours
- If pregnant do not take more than 10 tablets in 24 hours.
- do not use the maximum dosage for more than 2 weeks except under the advice and supervision of a doctor.

Directions

- adults and children 12 years of age and over: Chew 2-4 tablets completely as symptoms occur, or as directed by a doctor.
- Do not swallow tablets whole
- Do not take for symptoms that persist for more than 2 weeks unless advised by a doctor.

Other Information

- each tablet contains: Calcium 200mg
- Store below 30°C (86°F).
- Keep the container tightly closed

Inactive ingredients

adipic acid, D&C Red No. 27, D&C Yellow No. 10 Lake, dextrose, FD&C Blue No. 1 Lake, FD&C Yellow No. 6 Lake, flavors, magnesium stearate, maltodextrin, starch, sucralose.

SAFETY SEALED: DO NOT USE IF PRINTED SEAL UNDER CAP IS TORN OR MISSING.

Questions or comments?

1-866-467-2748

Package/Label Principal Display Panel

Compare to the active ingredients in Regular Strength Tums®

NDC 83324-315-15

Quality Choice

Regular Strength

Antacid Tablets

Calcium Carbonate 500mg

Relieves:

Upset Stomach

Heartburn

Acid Indigestion

Assorted Fruit

Naturally and artificially Flavored

150 Chewable Tablets

GLUTEN-FREE

Distributed by CDMA, INC

Novi, MI 48375

www.qualitychoice .com

Questions: 800-935-2362

*This product is not manufactured or distributed by GlaxoSmithKline LLC, owner of the registered trademark, Regular Strength Tums®

Quality Choice Regular Strength Antacid Tablets